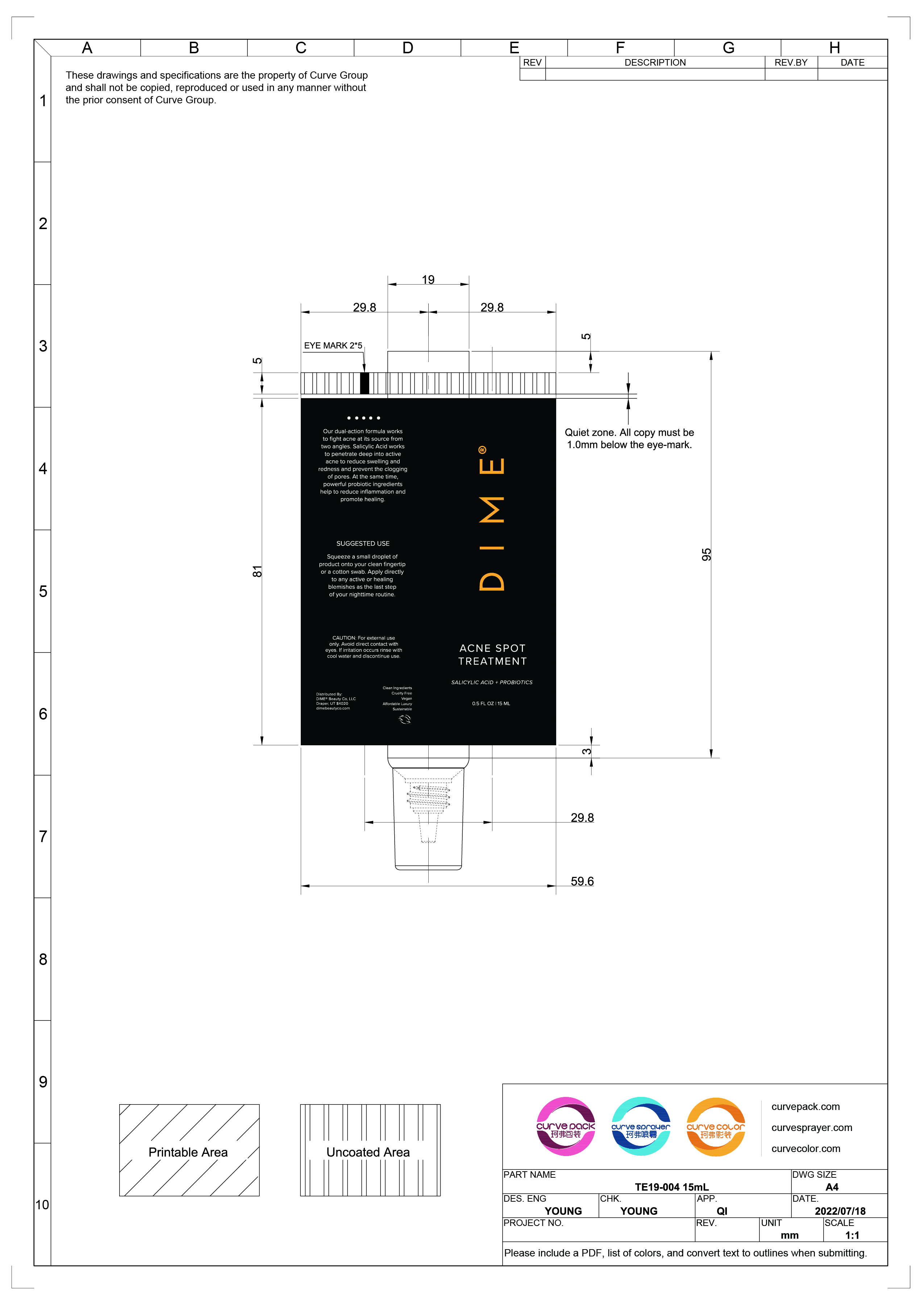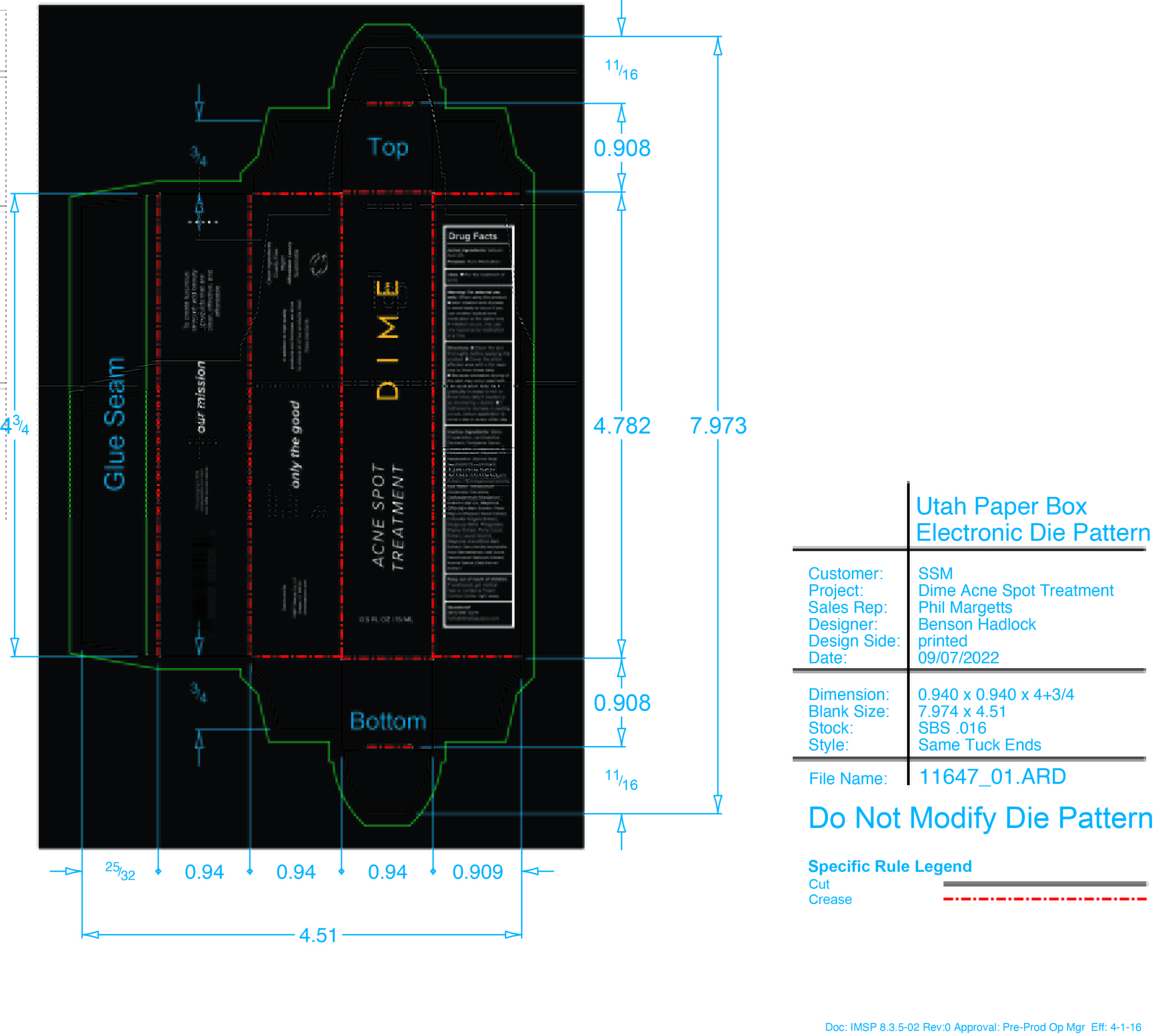 DRUG LABEL: Acne Spot Treatment
NDC: 82870-006 | Form: CREAM
Manufacturer: Dime Beauty Co, LLC
Category: otc | Type: HUMAN OTC DRUG LABEL
Date: 20251001

ACTIVE INGREDIENTS: SALICYLIC ACID 2 g/100 mL
INACTIVE INGREDIENTS: ARTEMISIA VULGARIS ROOT; MANUKA OIL; MAGNOLIA OFFICINALIS BARK; MAGNOLIA GRANDIFLORA BARK; HYDROXYACETOPHENONE; SODIUM HYDROXIDE; FU LING; PROPANEDIOL; CHLORELLA VULGARIS; HELICHRYSUM ITALICUM FLOWER; WHITE PEPPER; LIMOSILACTOBACILLUS FERMENTUM; PROPYLENE GLYCOL; AMMONIUM ACRYLOYLDIMETHYLTAURATE, DIMETHYLACRYLAMIDE, LAURYL METHACRYLATE AND LAURETH-4 METHACRYLATE COPOLYMER, TRIMETHYLOLPROPANE TRIACRYLATE CROSSLINKED (45000 MPA.S); SODIUM CHLORIDE; DICAPRYLYL ETHER; WATER; OAT; ALOE VERA LEAF; SACCHARIDE ISOMERATE; 1,2-HEXANEDIOL; SOYBEAN OIL; LAMINARIA DIGITATA; LAURYL ALCOHOL; OCTYLDODECANOL; GLYCERIN; TETRASODIUM GLUTAMATE DIACETATE

Acne Spot Treatment

Active Ingredients: Salicylic Acid 2%

Purpose: Acne medication

PURPOSE

Uses: For the treatment of acne

Keep out of reach of children. If swallowed, get medical help ro contact a Poison Control Center right away.

INDICATIONS AND USAGE

Skin irritation and dryness is more likely to occur if you use another topical acne medication at the same time. If irritation occurs, only use one topical acne medication at a time.

WARNINGS

Warning: For external use only

Directions:

- Clean the skin thoroughly before applying this product
- Cover the entire affected area with a thin layer one to three times daily.
- Because excessive drying of the skin may occur, start with one application daily, then gradually increase to two or three times daily or as directed by a doctor
- If bothersome dryness or peeling occurs reduce application to once a day or every other day

INACTIVE INGREDIENT

Inactive ingredients: Water, Propanediol, Lactobacillus Ferment, Pentylene Glycol, Polyacrylate Crosspolymer-6, Octyldodecanol, Glycerin, 1,2-Hexanediol, Glycine Soja (Soybean) Oil, Laminaria Digitata Extract, Sodium Hydroxide, Artemisia Vulgaris Extract, Hydroxyacetophenone, Sea Water, Tetrasodium Glutamate Diacetate, Leptospermum Scoparium Branch/Leaf Oil, Magnolia Officinalis Bark Extract, Piper Nigrum (Pepper) Seed Extract, Chlorella Vulgaris Extract, Dicaprylyl Ether, Phragmites Kharka Extract, Poria Cocos Extract, Lauryl Alcohol, Magnolia Grandiflora Bark Extract, Saccharide Isomerate, Aloe Barbadensis Leaf Juice, Helichrysum Italicum Extract, Avena Sativa (Oat) Kernel Extract

Questions?

(801) 996-8274

hello@dimebeautyco.com

PACKAGE LABEL

DIME

ACNE SPOT TREATMENT

SALICYLIC ACID + PROBIOTICS

0.5 FL OZ | 15 ML